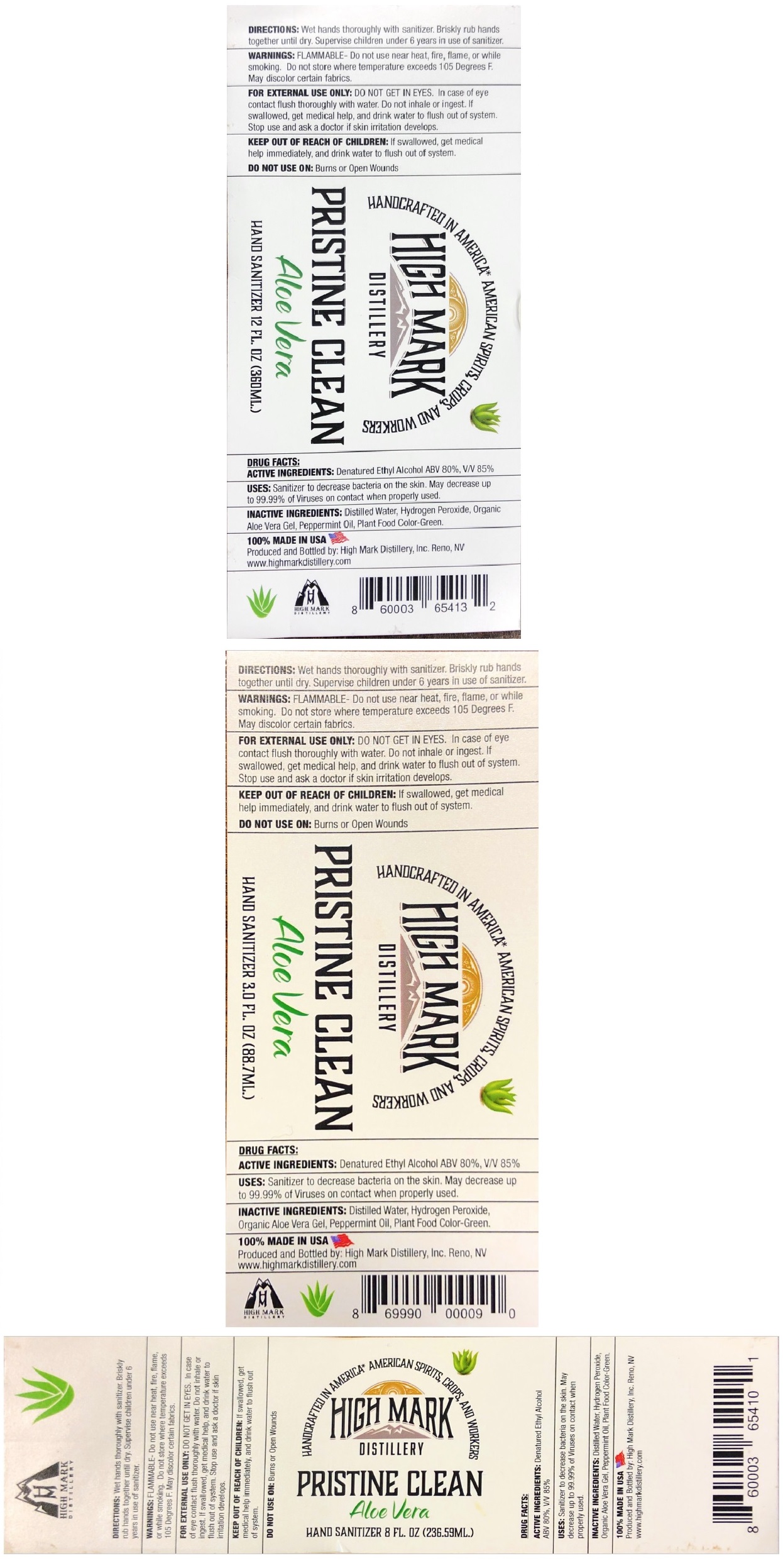 DRUG LABEL: Pristine Clean Hand Sanitizer- Aloe Vera
NDC: 78288-101 | Form: LIQUID
Manufacturer: High Mark Distillery, Inc. DBA: High Mark Barrel House, Inc.
Category: otc | Type: HUMAN OTC DRUG LABEL
Date: 20200609

ACTIVE INGREDIENTS: ALCOHOL 80 mL/100 mL
INACTIVE INGREDIENTS: WATER; HYDROGEN PEROXIDE; ALOE VERA LEAF; PEPPERMINT OIL; FD&C YELLOW NO. 5; FD&C BLUE NO. 1

HIGH MARK DISTILLERY PRISTINE CLEAN Aloe Vera HAND SANITIZER

ACTIVE INGREDIENTS:

Denatured Ethyl Alcohol ABV 80%

PURPOSE:

Antiseptic

INDICATIONS AND USAGE

USES: Sanitizer to decrease bacteria on the skin. May decrease up to 99.99% of Viruses on contact when properly used.

DOSAGE AND ADMINISTRATION

DIRECTIONS: Wet hands thoroughly with sanitizer. Briskly rub hands together until dry. Supervise children under 6 years in use of sanitizer.

WARNINGS

WARNINGS: FLAMMABLE- Do not use near heat, fire, flame, or while smoking. Do not store where temperature exceeds 105 Degrees F. May discolor certain fabrics.

FOR EXTERNAL USE ONLY: DO NOT GET IN EYES. In case of eye contact flush thoroughly with water. Do not inhale or ingest. If swallowed, get medical help, and drink water to flush out of system. Stop use and ask a doctor if skin irritation develops.

DO NOT USE ON: Burns or Open Wounds

KEEP OUT OF REACH OF CHILDREN: If swallowed, get medical help immediately, and drink water to flush out of system.

INACTIVE INGREDIENT

INACTIVE INGREDIENTS: Distilled Water, Hydrogen Peroxide, Organic Aloe Vera Gel, Peppermint Oil, Plant Food Color-Green.

HANDCRAFTED IN AMERICA* AMERICAN SPIRITS, CROPS, AND WORKERS

HIGH MARK DISTILLERY

100% MADE IN USA

Produced and Bottled by: High Mark Distillery; Inc. Reno, NV

www.highmarkdistillery.com